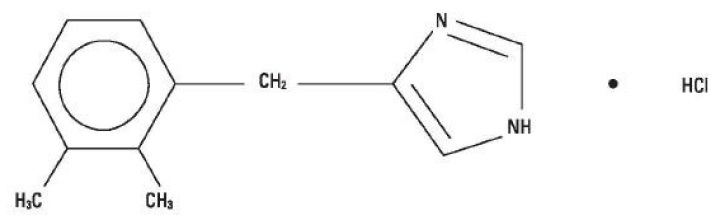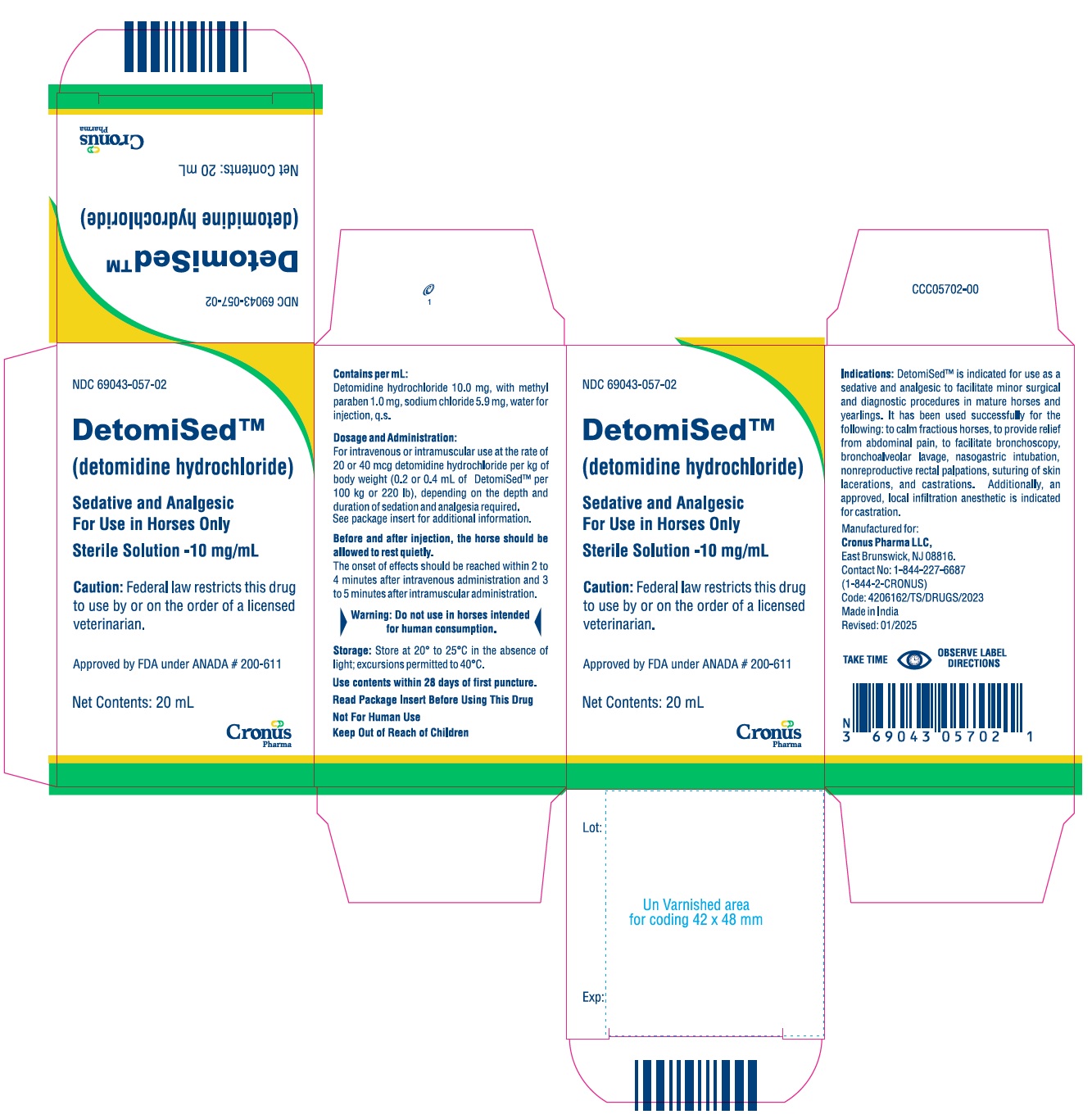 DRUG LABEL: DetomiSed
NDC: 69043-057 | Form: INJECTION
Manufacturer: Cronus Pharma LLC
Category: animal | Type: PRESCRIPTION ANIMAL DRUG LABEL
Date: 20250402

ACTIVE INGREDIENTS: DETOMIDINE HYDROCHLORIDE 10.0 mg/1 mL

DetomiSedTM
(detomidine hydrochloride)

Sedative and Analgesic For Use in Horses Only

Sterile solution

10 mg/mL

CAUTION: Federal law restricts this drug to use by or on the order of a licensed veterinarian.

DESCRIPTION

DESCRIPTION: DetomiSedTM is a synthetic alpha-2 adrenoreceptor agonist with sedative and analgesic properties. The chemical name is 1H imidazole, 4-[(2,3-dimethylphenyl) methyl]-hydrochloride and the generic name is detomidine hydrochloride. It is a white, crystalline, water-soluble substance having a molecular weight of 222.7. The molecular formula is C12H14N2∙HCl.

CHEMICAL STRUCTURE

Each mL of DetomiSed™ contains 10.0 mg detomidine hydrochloride, 1.0 mg methyl paraben, 5.9 mg sodium chloride, and water for injection, q.s.

CLINICAL PHARMACOLOGY

CLINICAL PHARMACOLOGY: DetomiSed™, a non-narcotic sedative and analgesic, is a potent α2-adrenoreceptor agonist which produces sedation and superficial and visceral analgesia which is dose dependent in its depth and duration. Profound lethargy and a characteristic lowering of the head with reduced sensitivity to environmental stimuli (sounds, etc.) are seen with detomidine. A short period of incoordination is characteristically followed by immobility and a firm stance with front legs well spread. The analgesic effect is most readily seen as an increase in the pain threshold at the body surface. Sensitivity to touch is little affected and in some cases may actually be enhanced.

With detomidine administration, heart rate is markedly decreased, blood pressure is initially elevated, and then a steady decline to normal is seen. A transient change in the conductivity of the cardiac muscle may occur, as evidenced by partial atrioventricular (AV) and sinoauricular (SA) blocks. This change in the conductivity of the cardiac muscle may be prevented by IV administration of atropine at 0.02 mg/kg of body weight.

No effect on blood clotting time or other hematological parameters was encountered at dosages of 20 or 40 mcg/kg of body weight. Respiratory responses include an initial slowing of respiration within a few seconds to 1 to 2 minutes after administration, increasing to normal within 5 minutes. An initial decrease in tidal volume is followed by an increase.

INDICATIONS AND USAGE

INDICATIONS: DetomiSed™ is indicated for use as a sedative and analgesic to facilitate minor surgical and diagnostic procedures in mature horses and yearlings. It has been used successfully for the following: to calm fractious horses, to provide relief from abdominal pain, to facilitate bronchoscopy, bronchoalveolar lavage, nasogastric intubation, nonreproductive rectal palpations, suturing of skin lacerations, and castrations. Additionally, an approved, local infiltration anesthetic is indicated for castration.

CONTRAINDICATIONS

CONTRAINDICATIONS: DetomiSed™ should not be used in horses with pre-existing AV or SA block, with severe coronary insufficiency, cerebrovascular disease, respiratory disease, or chronic renal failure. Intravenous potentiated sulfonamides should not be used in anesthetized or sedated horses as potentially fatal dysrhythmias may occur.

Information on the possible effects of detomidine hydrochloride in breeding horses is limited to uncontrolled clinical reports; therefore, this drug is not recommended for use in breeding animals.

WARNINGS

►WARNINGS: Do not use in horses intended for human consumption. Not for human use. Keep out of reach of children.◄

OTHER SAFETY INFORMATION

HUMAN SAFETY INFORMATION: Care should be taken to assure that detomidine hydrochloride is not inadvertently ingested as safety studies have indicated that the drug is well absorbed when administered orally. Standard ocular irritation tests in rabbits using the proposed market formulation have shown detomidine hydrochloride to be nonirritating to eyes. Primary dermal irritation tests in guinea pigs using up to 5 times the proposed market concentration of detomidine hydrochloride on intact and abraded skin have demonstrated that the drug is nonirritating to skin and is apparently poorly absorbed dermally. However, in accordance with prudent clinical procedures, exposure of eyes or skin should be avoided and affected areas should be washed immediately if exposure does occur. As with all injectable drugs causing profound physiological effects, routine precautions should be employed by practitioners when handling and using loaded syringes to prevent accidental self-injection.

PRECAUTIONS

PRECAUTIONS: Before administration, careful consideration should be given to administering DetomiSed™ to horses approaching or in endotoxic or traumatic shock, to horses with advanced liver or kidney disease, or to horses under stress from extreme heat, cold, fatigue, or high altitude. Protect treated horses from temperature extremes. Some horses, although apparently deeply sedated, may still respond to external stimuli. Routine safety measures should be employed to protect practitioners and handlers. Allowing the horse to stand quietly for 5 minutes before administration and for 10 to 15 minutes after injection may improve the response to DetomiSed™.

DetomiSed™ is a potent α2-agonist, and extreme caution should be exercised in its use with other sedative or analgesic drugs for they may produce additive effects.

When using any analgesic to help alleviate abdominal pain, a complete physical examination and diagnostic work-up are necessary to determine the etiology of the pain.

Food and water should be withheld until the sedative effect of DetomiSed™ has worn off.

ADVERSE REACTIONS

ADVERSE REACTIONS: Occasional reports of anaphylactic-like reactions have been received, including 1 or more of the following: urticaria, skin plaques, dyspnea, edema of the upper airways, trembling, recumbency, and death. The use of epinephrine should be avoided since epinephrine may potentiate the effects of α2-agonists. Reports of mild adverse reactions have resolved uneventfully without treatment. Severe adverse reactions should be treated symptomatically. As with all α2-agonists, the potential for isolated cases of hypersensitivity exist, including paradoxical response (excitation).

Contact Information

To report suspected adverse drug experience, for technical assistance or to obtain a copy of the Safety Data Sheet, contact Cronus Pharma LLC at 1-844-227-6687 or 1-844-2-CRONUS.

For additional information about adverse drug experience reporting for animal drugs, contact FDA at 1-888-FDA-VETS or http://www.fda.gov/reportanimalae

SIDE EFFECTS: Horses treated with DetomiSed™ exhibit hypertension. Bradycardia routinely occurs 1 minute after injection. The relationship between hypertension and bradycardia is consistent with an adaptive baroreceptor response to the increased pressure and inconsistent with a primary drug-induced bradycardia. Piloerection, sweating, salivation, and slight muscle tremors are frequently seen after administration. Partial transient penis prolapse may be seen. Partial AV and SA blocks may occur with decreased heart and respiratory rates. Urination typically occurs during recovery at about 45 to 60 minutes posttreatment, depending on dosage. Incoordination or staggering is usually seen only during the first 3 to 5 minutes after injection, until animals have secured a firm footing.

Because of continued lowering of the head during sedation, mucus discharges from the nose and, occasionally, edema of the head and face may be seen. Holding the head in a slightly elevated position generally prevents these effects.

OVERDOSAGE

OVERDOSAGE: Detomidine hydrochloride is tolerated in horses at up to 200 mcg/kg of body weight (10 times the low dosage and 5 times the high dosage). In safety studies in horses, detomidine hydrochloride at 400 mcg/kg of body weight administered daily for 3 consecutive days produced microscopic foci of myocardial necrosis in 1 of 8 horses.

DOSAGE AND ADMINISTRATION:

For Sedation: Administer DetomiSed™ IV or IM at the rates of 20 or 40 mcg detomidine hydrochloride per kg of body weight (0.2 or 0.4 mL of DetomiSed™ per 100 kg or 220 lb), depending on the depth and duration of sedation required. Onset of sedative effects should be reached within 2 to 4 minutes after IV administration and 3 to 5 minutes after IM administration. Twenty mcg/kg will provide 30 to 90 minutes of sedation and 40 mcg/kg will provide approximately 90 minutes to 2 hours of sedation.

For Analgesia: Administer DetomiSed™ IV at the rates of 20 or 40 mcg detomidine hydrochloride per kg of body weight (0.2 or 0.4 mL of DetomiSed™ per 100 kg or 220 lb), depending on the depth and duration of analgesia required. Twenty mcg/kg will usually begin to take effect in 2 to 4 minutes and provide 30 to 45 minutes of analgesia. The 40 mcg/kg dose will also begin to take effect in 2 to 4 minutes and provide 45 to 75 minutes of analgesia.

For Both Sedation and Analgesia: Administer DetomiSed™ IV at the rates of 20 or 40 mcg detomidine hydrochloride per kg of body weight (0.2 or 0.4 mL of DetomiSed™ per 100 kg or 220 lb), depending on the depth and duration of sedation and analgesia required.

Before and after injection, the animal should be allowed to rest quietly.

STORAGE AND HANDLING

STORAGE: Store at (20° to 25°C) in the absence of light; excursions permitted to 40°C.

Use contents within 28 days of first puncture.

HOW SUPPLIED

HOW SUPPLIED: DetomiSed™ is supplied in 20 mL multi-dose vials.

NDC 69043-057-02, 20 mL vial in package of one.

Approved by FDA under ANADA # 200-611

Manufactured for:
Cronus Pharma LLC,
East Brunswick, NJ 08816.
Contact No: 1-844-227-6687
(1-844-2-CRONUS)

Made in India

Revised: 01/2025

PACKAGE LABEL.PRINCIPAL DISPLAY PANEL

NDC 69043-057-02

DetomiSedTM

(detomidine hydrochloride)

Sedative and Analgesic
For Use in Horses Only

Sterile Solution - 10 mg/mL

Caution: Federal law restricts this drug to use by or on the order of a licensed veterinarian.

Approved by FDA under ANADA # 200-611

Net Contents: 20 mL